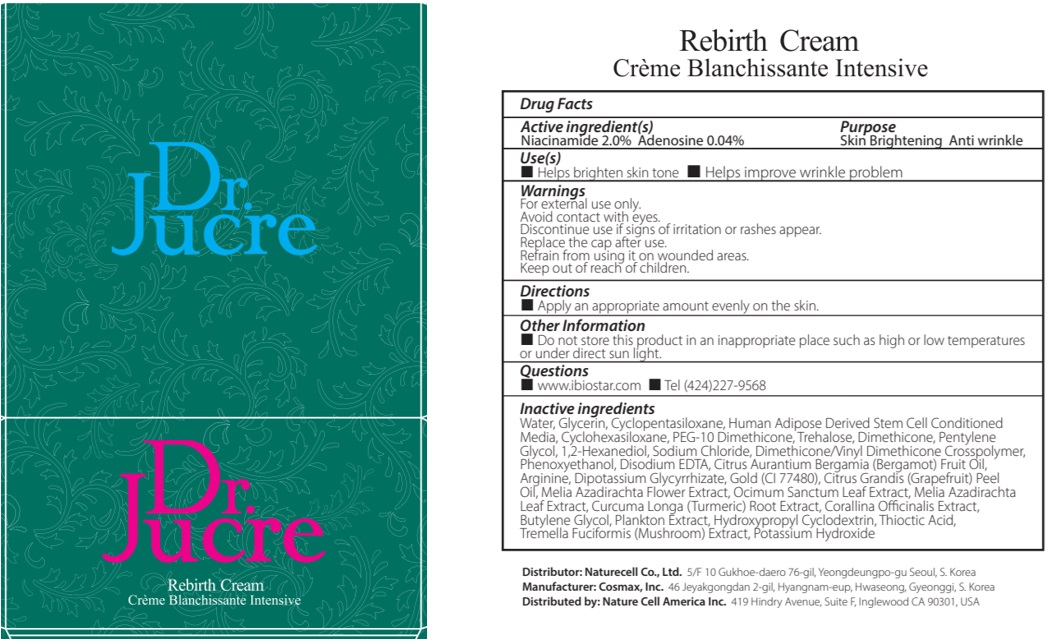 DRUG LABEL: Dr.Jucre Rebirth
NDC: 83071-130 | Form: CREAM
Manufacturer: NATURECELL CO., LTD.
Category: otc | Type: HUMAN OTC DRUG LABEL
Date: 20250102

ACTIVE INGREDIENTS: NIACINAMIDE 2 g/100 mL; ADENOSINE 0.04 g/100 mL
INACTIVE INGREDIENTS: WATER; GLYCERIN; CYCLOMETHICONE 5

ACTIVE INGREDIENTS

Niacinamide 2.0%
Adenosine 0.04%

INACTIVE INGREDIENTS

Water, Glycerin, Cyclopentasiloxane, Human Adipose Derived Stem Cell Conditioned Media, Cyclohexasiloxane, PEG-10 Dimethicone, Trehalose, Dimethicone, Pentylene Glycol, 1,2-Hexanediol, Sodium Chloride, Dimethicone/Vinyl Dimethicone Crosspolymer, Phenoxyethanol, Disodium EDTA, Citrus Aurantium Bergamia (Bergamot) Fruit Oil, Arginine, Dipotassium Glycyrrhizate, Gold (CI 77480), Citrus Grandis (Grapefruit) Peel Oil, Melia Azadirachta Flower Extract, Ocimum Sanctum Leaf Extract, Melia Azadirachta Leaf Extract, Curcuma Longa (Turmeric) Root Extract, Corallina Officinalis Extract, Butylene Glycol, Plankton Extract, Hydroxypropyl Cyclodextrin, Thioctic Acid, Tremella Fuciformis (Mushroom) Extract, Potassium Hydroxide

PURPOSE

Skin Brightening
Anti wrinkle

WARNINGS

For external use only.
Avoid contact with eyes.
Discontinue use if signs of irritation or rashes appear.
Replace the cap after use.
Refrain from using it on wounded areas.
Keep out of reach of children.

KEEP OUT OF REACH OF CHILDREN

Keep out of the reach of children.

Uses

■ Helps brighten skin tone
■ Helps improve wrinkle problem

Directions

■ Apply an appropriate amount evenly on the skin.

Other Information

■ Do not store this product in an inappropriate place such as high or low temperatures or under direct sun light.

Questions

■ www.ibiostar.com
■ Tel (424)227-9568